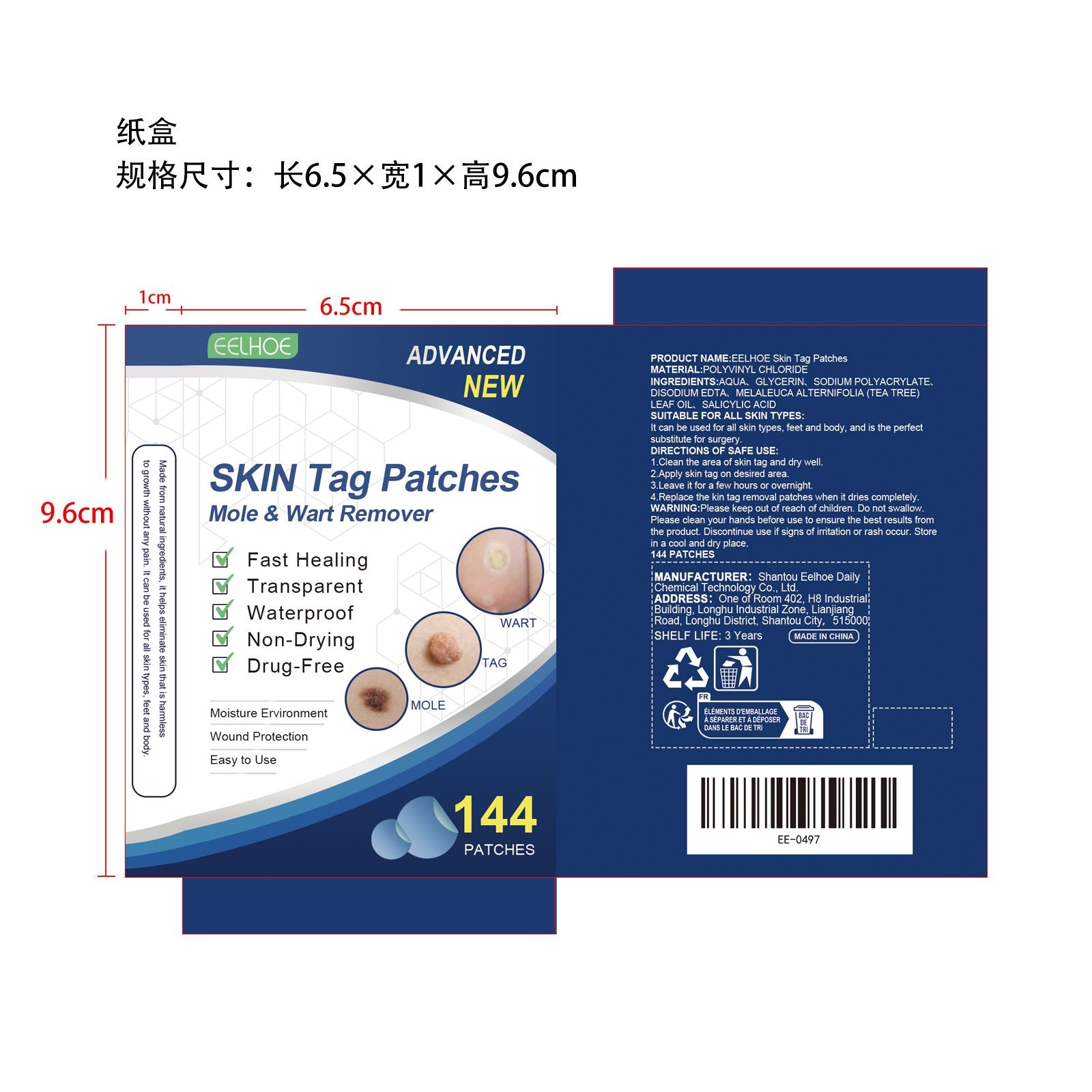 DRUG LABEL: EELHOE Skin Tag Patches
NDC: 85064-011 | Form: PATCH
Manufacturer: Shantou Eelhoe Daily Chemical Technology Co., Ltd.
Category: otc | Type: HUMAN OTC DRUG LABEL
Date: 20251127

ACTIVE INGREDIENTS: MELALEUCA ALTERNIFOLIA (TEA TREE) LEAF OIL 0.144 mg/144 mg
INACTIVE INGREDIENTS: AQUA 107.6832 mg/144 mg; EDETATE DISODIUM 0.144 mg/144 mg; SODIUM POLYACRYLATE (8000 MW) 7.2 mg/144 mg; SALICYLIC ACID 0.0288 mg/144 mg; GLYCERIN 28.8 mg/144 mg

ACTIVE INGREDIENT

MELALEUCA ALTERNIFOLIA (TEA TREE) LEAF OIL

WHEN USING

1.Clean the area of skin tag and dry well.

2.Apply skin tag on desired area.

3.Leave it for a few hours or overnight.

4.Replace the kin tag removal patches when it dries completely.

PURPOSE

Fast Healing
Transparent
Waterproof
Non-Drying
Drug-Free

WARNINGS

Please keep out of reach of children. Do not swallow.Please clean your hands before use to ensure the best results from the product. Discontinue use if signs of irritation or rash occur. Store in a cool and dry place.

DO NOT USE

Discontinue use if signs of irritation or rash occur.

STOP USE

Discontinue use if signs of irritation or rash occur.

KEEP OUT OF REACH OF CHILDREN

Please keep out of reach of children. Do not swallow.

STORAGE AND HANDLING

Store in a cool and dry place.

INACTIVE INGREDIENT

AQUA、GLYCERIN、SODIUM POLYACRYLATE、DISODIUM EDTA、SALICYLIC ACID

DOSAGE AND ADMINISTRATION

1.Clean the area of skin tag and dry well.

2.Apply skin tag on desired area.

3.Leave it for a few hours or overnight.

4.Replace the kin tag removal patches when it dries completely.

INDICATIONS AND USAGE

1.Clean the area of skin tag and dry well.

2.Apply skin tag on desired area.

3.Leave it for a few hours or overnight.

4.Replace the kin tag removal patches when it dries completely.